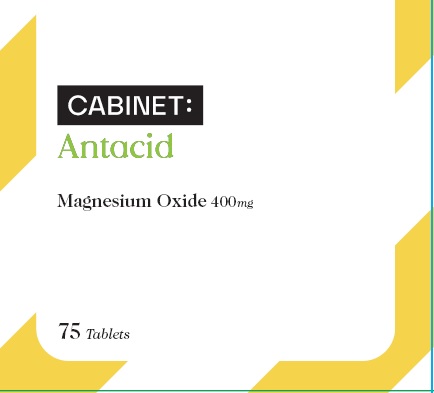 DRUG LABEL: Magnesium Oxide 400mg
NDC: 68210-4105 | Form: TABLET
Manufacturer: Spirit Pharmaceuticals LLC
Category: otc | Type: HUMAN OTC DRUG LABEL
Date: 20241213

ACTIVE INGREDIENTS: MAGNESIUM OXIDE 400 mg/1 1
INACTIVE INGREDIENTS: SILICON DIOXIDE; CROSCARMELLOSE SODIUM; CELLULOSE, MICROCRYSTALLINE; STEARIC ACID

Magnesium Oxide Tablets

ACTIVE INGREDIENT (In each tablet)

Magnesium Oxide 400mg (241.3mg elemental magnesium)

Purpose

Antacid

USES

relieves

- acid indigestion
- upset stomach

WARNINGS

Ask a doctor if you have

kidney disease

Ask a doctor or pharmacist before use if you are

taking a prescription drug. Antacids may interact with certain prescription drugs.

Do not take

more than 2 tablets in a 24 hour period or use the maximum dosage of this product for more than two weeks, except under the advise and supervision of a physician. May have a laxative effect.

If pregnant or breast-feeding,

ask a health professional before use.

Keep out of reach of children.

DIRECTIONS

- take 1 tablet twice a day or as directed by a physician

OTHER INFORMATION

- Magnesium content per tablet: 241.3mg
- store at room temperature 59°-86° F (15°-30°C)

INACTIVE INGREDIENTS

colloidal silicon dioxide, croscarmellose sodium, microcrystalline cellulose, stearic acid

Questions or comments?

1-888-333-9792

PDP

Cabinet:

Antacid

Magnesium Oxide 400mg

75 Tablets